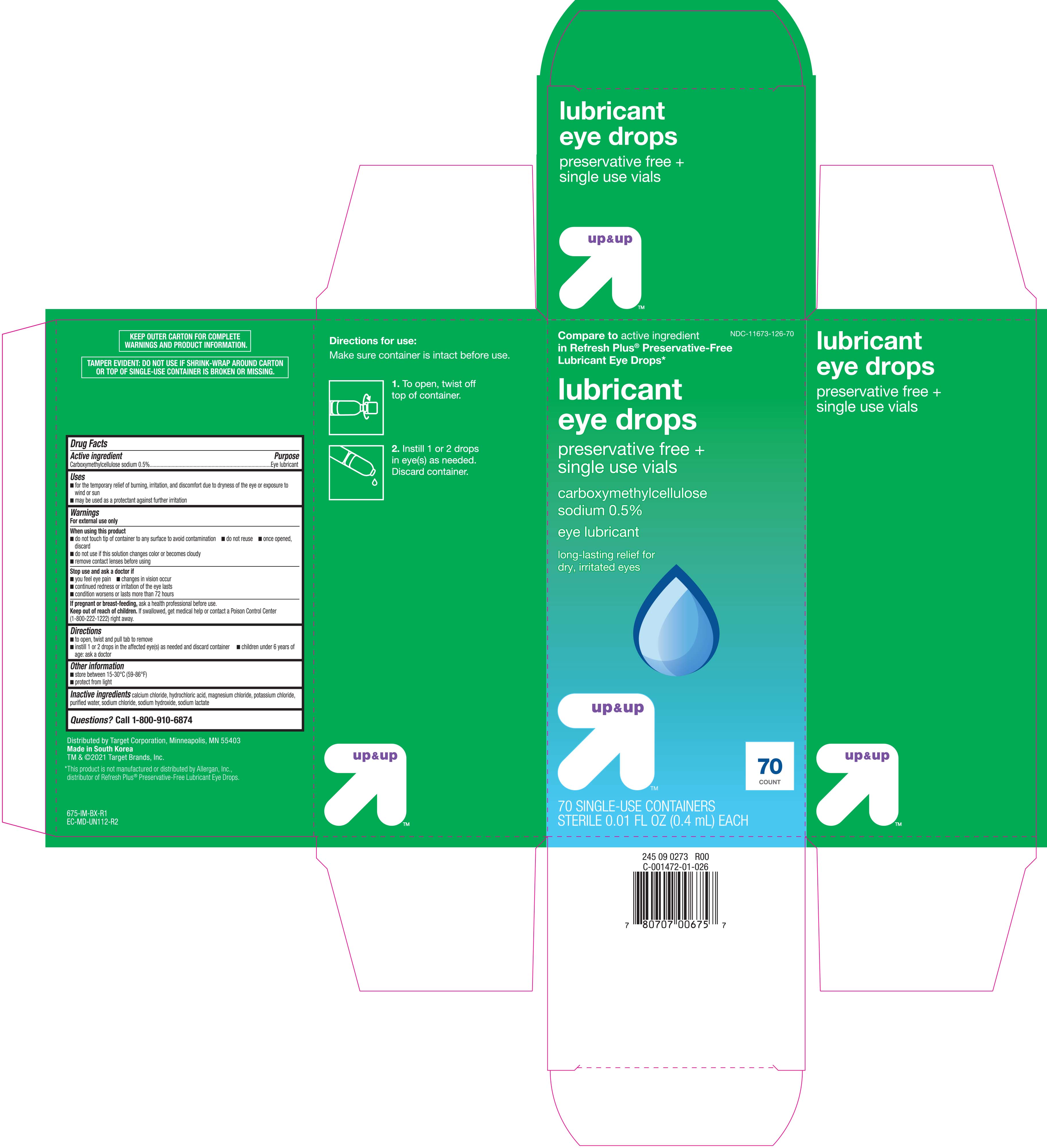 DRUG LABEL: Up and Up Lubricant
NDC: 11673-126 | Form: SOLUTION/ DROPS
Manufacturer: Target Corporation
Category: otc | Type: HUMAN OTC DRUG LABEL
Date: 20221215

ACTIVE INGREDIENTS: CARBOXYMETHYLCELLULOSE SODIUM 5 mg/1 mL
INACTIVE INGREDIENTS: CALCIUM CHLORIDE; HYDROCHLORIC ACID; WATER; SODIUM HYDROXIDE; SODIUM LACTATE; SODIUM CHLORIDE; POTASSIUM CHLORIDE; MAGNESIUM CHLORIDE

Up & Up Lubricant Single Use Eye Drops 70 ct. 675

Active ingredient Purpose

Carboxymethylcellulose sodium 0.5%................Eye lubricant

Uses

- for the temporary relief of burning, irritation, and discomfort due to dryness of the eye or exposure to wind or sun
- may be used as a protectant against further irritation

Warnings

For external use only

When using this product

- do not touch tip of container to any surface to avoid contamination
- do not reuse
- once opened, discard
- do not use if this solution changes color or becomes cloudy

Stop use and ask a doctor if

- you feel eye pain
- changes in vision occur
- continued redness or irritation of the eye lasts
- condition worsens or lasts more than 72 hours

PREGNANCY OR BREAST FEEDING

If pregnant or breast-feeding, ask a health professional before use.

KEEP OUT OF REACH OF CHILDREN

Keep out of reach children. If swallowed, get medical help or contact a Poison Control Center (1-800-222-1222) right away.

Directions

- to open, twist and pull tab to remove
- instill 1 or 2 drops in the affected eye(s) as needed and discard container
- children under 6 years of age: ask a doctor

Other information

- store between 15-30°C (59-86°F)
- protect from light

Inactive ingredients

calcium chloride, hydrochloric acid, magnesium chloride, potassium chloride. purified water, sodium chloride, sodium hydroxide, sodium lactate

DOSAGE AND ADMINISTRATION

Distributed by Target Corporation

Made in South Korea